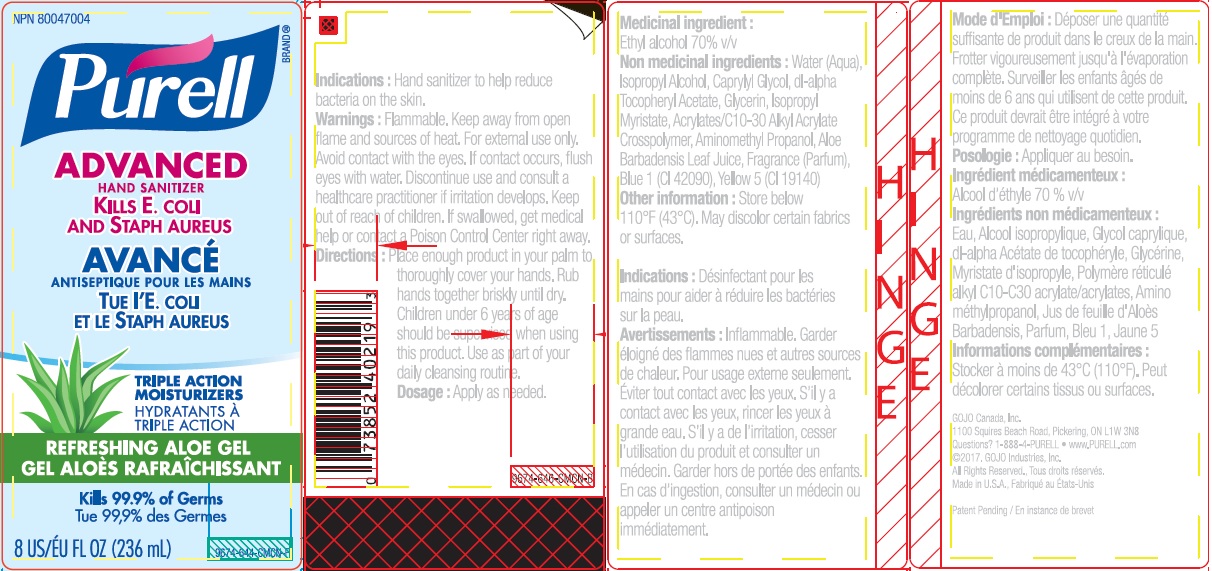 DRUG LABEL: PURELL Advanced Instant Hand Sanitiser Aloe Gel
NDC: 21749-733 | Form: GEL
Manufacturer: GOJO Industries, Inc.
Category: otc | Type: HUMAN OTC DRUG LABEL
Date: 20250702

ACTIVE INGREDIENTS: ALCOHOL 0.7 mL/1 mL
INACTIVE INGREDIENTS: WATER; ISOPROPYL ALCOHOL; ALOE VERA LEAF; CAPRYLYL GLYCOL; GLYCERIN; ISOPROPYL MYRISTATE; .ALPHA.-TOCOPHEROL ACETATE, D-; AMINOMETHYLPROPANOL; FD&C BLUE NO. 1; FD&C YELLOW NO. 5

PURELL Advanced Instant Hand Sanitiser Aloe Gel